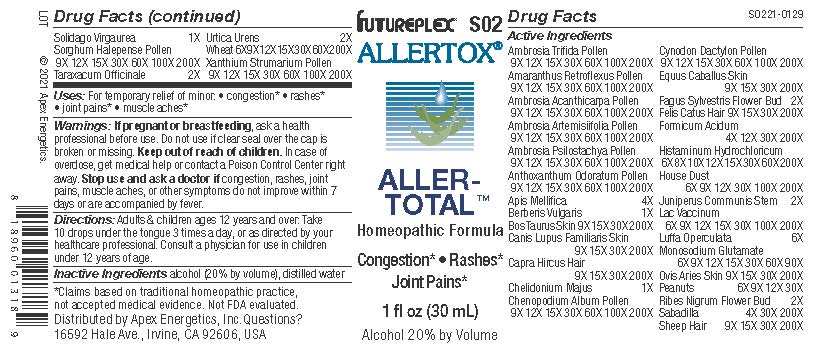 DRUG LABEL: S02
NDC: 63479-1902 | Form: SOLUTION/ DROPS
Manufacturer: Apex Energetics Inc.
Category: homeopathic | Type: HUMAN OTC DRUG LABEL
Date: 20240108

ACTIVE INGREDIENTS: EQUUS CABALLUS SKIN 200 [hp_X]/1 mL; FORMIC ACID 200 [hp_X]/1 mL; HISTAMINE DIHYDROCHLORIDE 200 [hp_X]/1 mL; COW MILK 200 [hp_X]/1 mL; LUFFA OPERCULATA FRUIT 6 [hp_X]/1 mL; PEANUT 30 [hp_X]/1 mL; SCHOENOCAULON OFFICINALE SEED 200 [hp_X]/1 mL; SHEEP WOOL 200 [hp_X]/1 mL; SORGHUM HALEPENSE POLLEN 200 [hp_X]/1 mL; TARAXACUM OFFICINALE 2 [hp_X]/1 mL; WHEAT 200 [hp_X]/1 mL; XANTHIUM STRUMARIUM POLLEN 200 [hp_X]/1 mL; AMBROSIA ACANTHICARPA POLLEN 200 [hp_X]/1 mL; CHENOPODIUM ALBUM POLLEN 200 [hp_X]/1 mL; AMARANTHUS RETROFLEXUS POLLEN 200 [hp_X]/1 mL; CYNODON DACTYLON POLLEN 200 [hp_X]/1 mL; FAGUS SYLVATICA FLOWER BUD 2 [hp_X]/1 mL; FELIS CATUS HAIR 200 [hp_X]/1 mL; JUNIPERUS COMMUNIS STEM 2 [hp_X]/1 mL; APIS MELLIFERA 4 [hp_X]/1 mL; BERBERIS VULGARIS ROOT BARK 1 [hp_X]/1 mL; RIBES NIGRUM FLOWER BUD 2 [hp_X]/1 mL; CHELIDONIUM MAJUS 1 [hp_X]/1 mL; HOUSE DUST 200 [hp_X]/1 mL; MONOSODIUM GLUTAMATE 90 [hp_X]/1 mL; OVIS ARIES SKIN 200 [hp_X]/1 mL; SOLIDAGO VIRGAUREA FLOWERING TOP 1 [hp_X]/1 mL; URTICA URENS 2 [hp_X]/1 mL; AMBROSIA ARTEMISIIFOLIA POLLEN 200 [hp_X]/1 mL; AMBROSIA PSILOSTACHYA POLLEN 200 [hp_X]/1 mL; AMBROSIA TRIFIDA POLLEN 200 [hp_X]/1 mL; ANTHOXANTHUM ODORATUM POLLEN 200 [hp_X]/1 mL; BOS TAURUS SKIN 200 [hp_X]/1 mL; CANIS LUPUS FAMILIARIS SKIN 200 [hp_X]/1 mL; CAPRA HIRCUS HAIR 200 [hp_X]/1 mL
INACTIVE INGREDIENTS: ALCOHOL; WATER

S02

Active Ingredients
Amaranthus Retroflexus Pollen | 9X 12X 15X 30X 60X 100X 200X
Ambrosia Acanthicarpa Pollen | 9X 12X 15X 30X 60X 100X 200X
Ambrosia Artemisiifolia Pollen | 9X 12X 15X 30X 60X 100X 200X
Ambrosia Psilostachya Pollen | 9X 12X 15X 30X 60X 100X 200X
Ambrosia Trifida Pollen | 9X 12X 15X 30X 60X 100X 200X
Anthoxanthum Odoratum Pollen | 9X 12X 15X 30X 60X 100X 200X
Apis Mellifica | 4X
Berberis Vulgaris | 1X
Bos Taurus Skin | 9X 15X 30X 200X
Canis Lupus Familiaris Skin | 9X 15X 30X 200X
Capra Hircus Hair | 9X 15X 30X 200X
Chelidonium Majus | 1X
Chenopodium Album Pollen | 9X 12X 15X 30X 60X 100X 200X
Cynodon Dactylon Pollen | 9X 12X 15X 30X 60X 100X 200X
Equus Caballus Skin | 9X 15X 30X 200X
Fagus Sylvestris Flower Bud | 2X
Felis Catus Hair | 9X 15X 30X 200X
Formicum Acidum | 4X 12X 30X 200X
Histaminum Hydrochloricum | 6X 8X 10X 12X 15X 30X 60X 200X
House Dust | 6X 9X 12X 30X 100X 200X
Juniperus Communis Stem | 2X
Lac Vaccinum | 6X 9X 12X 15X 30X 100X 200X
Luffa Operculata | 6X
Monosodium Glutamate | 6X 9X 12X 15X 30X 60X 90X
Ovis Aries Skin | 9X 15X 30X 200X
Peanuts | 6X 9X 12X 30X
Ribes Nigrum Flower Bud | 2X
Sabadilla | 4X 30X 200X
Sheep Hair | 9X 15X 30X 200X
Solidago Virgaurea | 1X
Sorghum Halepense Pollen | 9X 12X 15X 30X 60X 100X 200X
Taraxacum Officinale | 2X
Urtica Urens | 2X
Wheat | 6X 9X 12X 15X 30X 60X 200X
Xanthium Strumarium Pollen | 9X 12X 15X 30X 60X 100X 200X

INDICATIONS AND USAGE

Uses:

For temporary relief of minor:

congestion*

rashes*

joint pains*

muscle aches*

*Claims based on traditional homeopathic practice, not accepted medical evidence. Not FDA evaluated.

Warnings:

PREGNANCY OR BREAST FEEDING

If pregnant or breastfeeding, ask a health professional before use.

Do not use if clear seal over the cap is broken or missing.

Keep out of reach of children. In case of overdose, get medical help or contact a Poison Control Center right away.

Stop use and ask a doctor if congestion, rashes, joint pains, muscle aches, or other symptoms do not improve within 7 days or are accompanied by fever.

Directions:

Adults & children ages 12 years and over: Take 10 drops under the tongue 3 times a day, or as directed by your healthcare professional. Consult a physician for use in children under 12 years of age.

Inactive Ingredients

alcohol (20% by volume), distilled water

Distributed by Apex Energetics, Inc.Questions?

16592 Hale Ave., Irvine, CA 92606, USA

PACKAGE LABEL

FUTUREPLEX® S02

ALLERTOX®

ALLERTOTAL™

Homeopathic Formula

Congestion* Rashes*

Joint Pains*

1 fl oz (30 mL)

Alcohol 20% by Volume